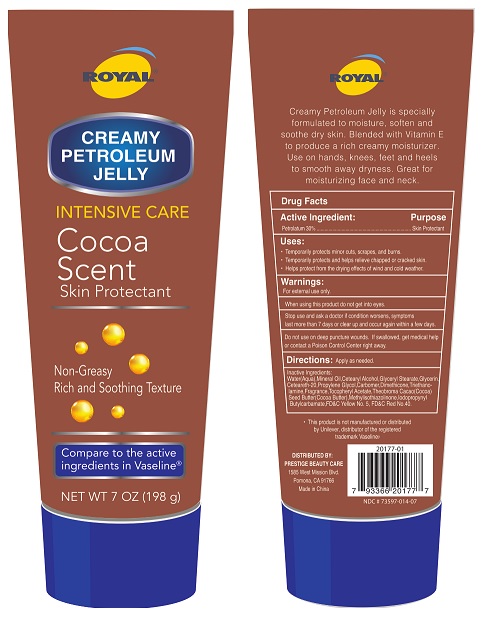 DRUG LABEL: Royal Creamy Petroleum Jelly Cocoa Butter
NDC: 73597-014 | Form: JELLY
Manufacturer: Mission Series Inc. dba Prestige Beauty Care
Category: otc | Type: HUMAN OTC DRUG LABEL
Date: 20250123

ACTIVE INGREDIENTS: PETROLATUM 30 g/100 g
INACTIVE INGREDIENTS: WATER; 2,2'-((2-(DODECYLOXY)ETHYL)IMINO)BISETHANOL; METHYLISOTHIAZOLINONE; FD&C YELLOW NO. 5; GLYCERYL MONOSTEARATE; POLYOXYL 20 CETOSTEARYL ETHER; CARBOMER HOMOPOLYMER TYPE C (ALLYL PENTAERYTHRITOL CROSSLINKED); COCOA BUTTER; IODOPROPYNYL BUTYLCARBAMATE; FD&C RED NO. 40; PROPYLENE GLYCOL; DIMETHICONE; .ALPHA.-TOCOPHEROL ACETATE; MINERAL OIL; CETOSTEARYL ALCOHOL; GLYCERIN

Royal Creamy Petroleum Jelly Cocoa Butter

Creamy Petroleum Jelly is specially formulated to moisturize, soften and sooth dry skin. Blended with Vitamin E to produce a rich creamy moisturizer. Use on hands, knees, feet and heels to smooth away dryness. Great for moisturizing face and neck.

Active Ingredient

Active Ingredient: Petrolatum 30%

Purpose

Purpose Skin Protectant

Indications & Usage

Uses:

Temporarily protects minor cuts, scrapes, and burns.

Temporarily protects and helps relieve chapped or cracked skin.

Helps protect from the drying effects of wind and cold weather.

Warnings

For external use only.

When using this product do not get into eyes.

Do not use on deep puncture wounds.

Stop Use

Stop use and ask a doctor if condition worsens, symptoms last more than 7 days or clear up and occur again within a few days.

Keep Out of Reach of Children. If swallowed, get medical help or contacit Poison Control Center right away.

Directions

Directions: Apply as needed.

Inactive Ingredients

Inactive Ingredients: Water (Aqua), Mineral Oil, Cetearyl Alcohol, Glyceryl Stearate, Glycerin, Ceteareth-20, Propylene Glycol, Carbomer, Dimethicone, Triethanolamine, Fragrance, Tocopheryl Acetate, Theobroma Cacao (Cocoa) Seed Butter (Cocoa Butter), Methylisothiazolinone, Iodopropynyl Butylcarbamate, FD&C Yellow No. 5, FD&C Red No. 40.

Made in China

DISTRIBUTED BY:

PRESTIGE BEAUTY CARE

1585 West Mission Blvd.

Pomona, CA 91766

* This product is not manufactured or distributed by Unilever, distributor of the registered trademark Vaseline(r).